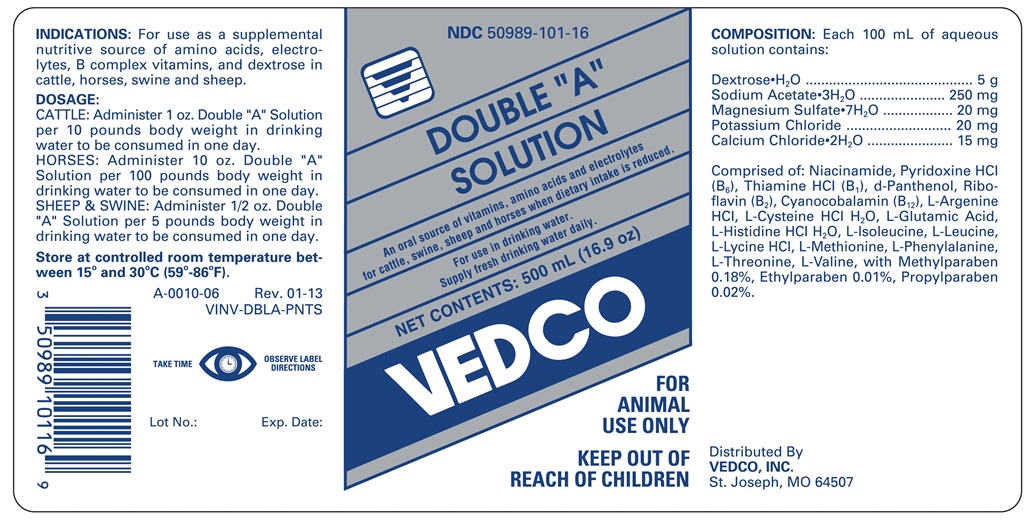 DRUG LABEL: Double A
NDC: 50989-101 | Form: SOLUTION
Manufacturer: Vedco, Inc.
Category: animal | Type: OTC ANIMAL DRUG LABEL
Date: 20170117

ACTIVE INGREDIENTS: DEXTROSE MONOHYDRATE 5000 mg/100 mL; CALCIUM CHLORIDE ANHYDROUS 15 mg/100 mL; MAGNESIUM SULFATE HEPTAHYDRATE 20  mg/100 mL; POTASSIUM CHLORIDE 20 mg/100 mL; SODIUM ACETATE ANHYDROUS 250 mg/100 mL
INACTIVE INGREDIENTS: VALINE

Double "A" Solution

INDICATIONS AND USAGE

An oral source of vitamins, amino acids and electrolytes for cattle, swine, sheep and horses when dietary intake is reduced.

For use in drinking water. Supply fresh drinking water daily.

INDICATIONS

For use as a supplemental nutritive source of amino acids, electrolytes, B complex vitamins, and dextrose in cattle, horses, swine and sheep.

DOSAGE

For use in drinking water. Supply fresh water daily.

Cattle: Administer 1 oz. Double "A" Solution per 10 pounds body weight in the drinking water consumed in one day.

Horses: Administer 10 oz. Double "A" Solution per 100 pounds body weight in the drinking water consumed in one day.

Sheep and Swine: Administer 1/2 oz. per 5 pounds body weight i the drinking water consume in one day.

STORAGE AND HANDLING

Store at controlled room temperature between 15o and 30oC (59o-86oF).

TAKE TIME OBSERVE LABEL DIRECTIONS

COMPOSITION

Each 100 mL of aqueous solution contains:

Dextrose•H2O ....................................... 5 g

Sodium Acetate•3H2O ..................... 250 mg

Magnesium Sulfate•7H2O .................. 20 mg

Potassium Chloride ........................... 20 mg

Calcium Chloride•2H2O ..................... 15 mg

Comprised of: Niacinamide, Pyridoxine HCl (B6), d-Panthenol, Riboflavin (B2), Cyanocobalamin (B12), L-Argenine HCl, L-Cysteine HCl H2O, L-Glutamic Acid, L-Histidine HCl H2O, L-Isoleucie, L-Leucine, L-Lycine HCl, L-Methionine, L-Phenylalamine, L-Theonine, L-Valine with Methylparaben 0.18%, Ethylparaben 0.01%, Propylparaben 0.02%.